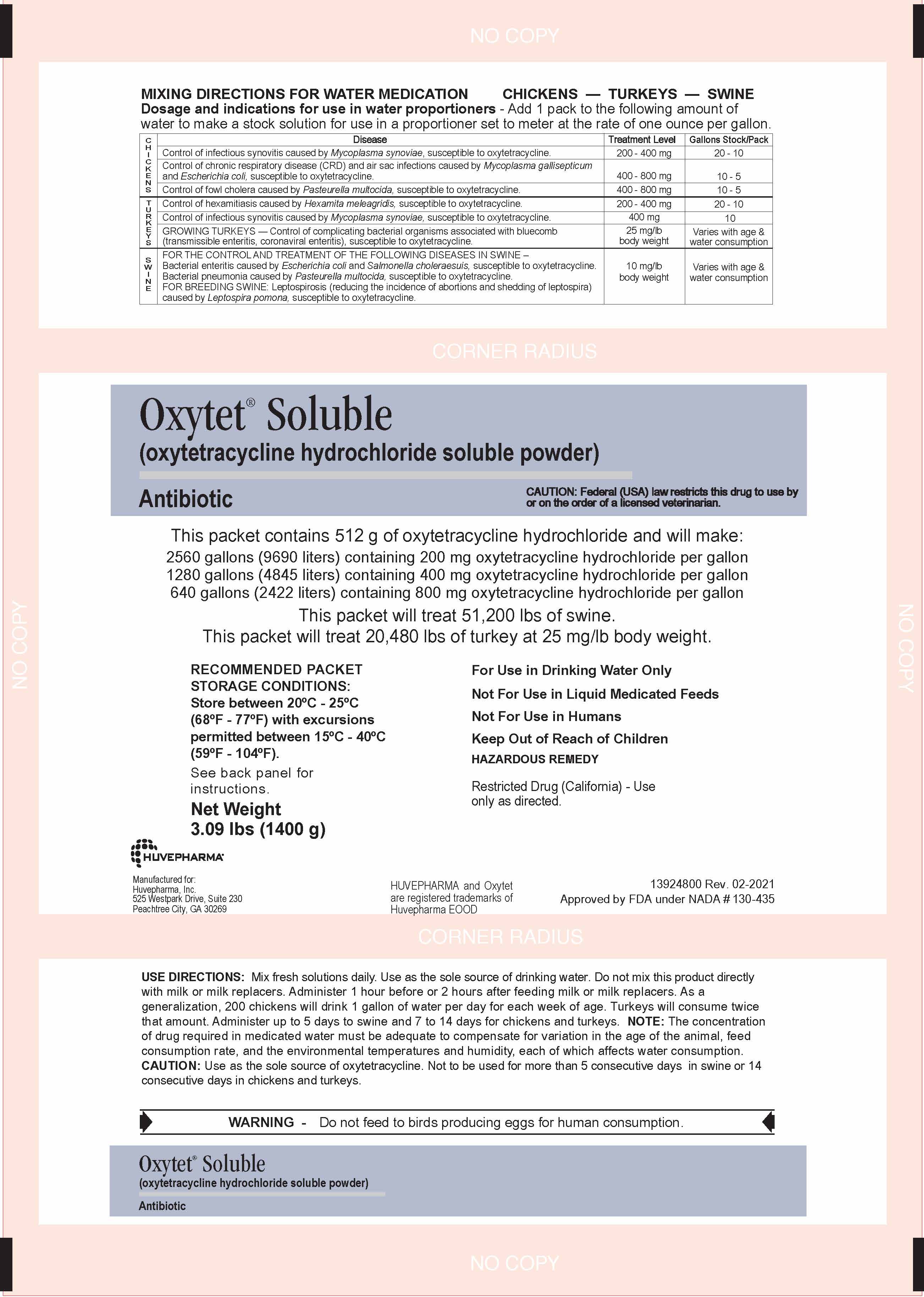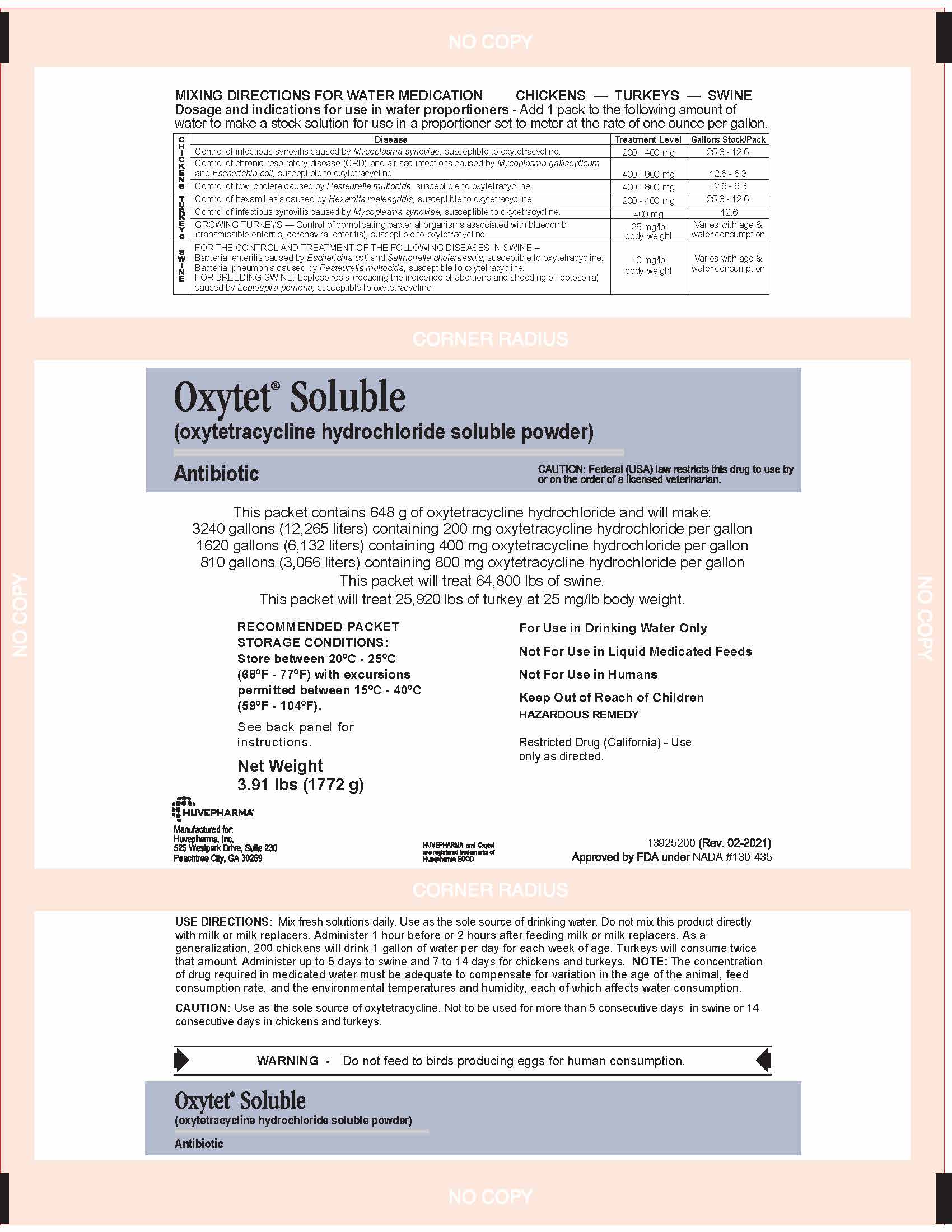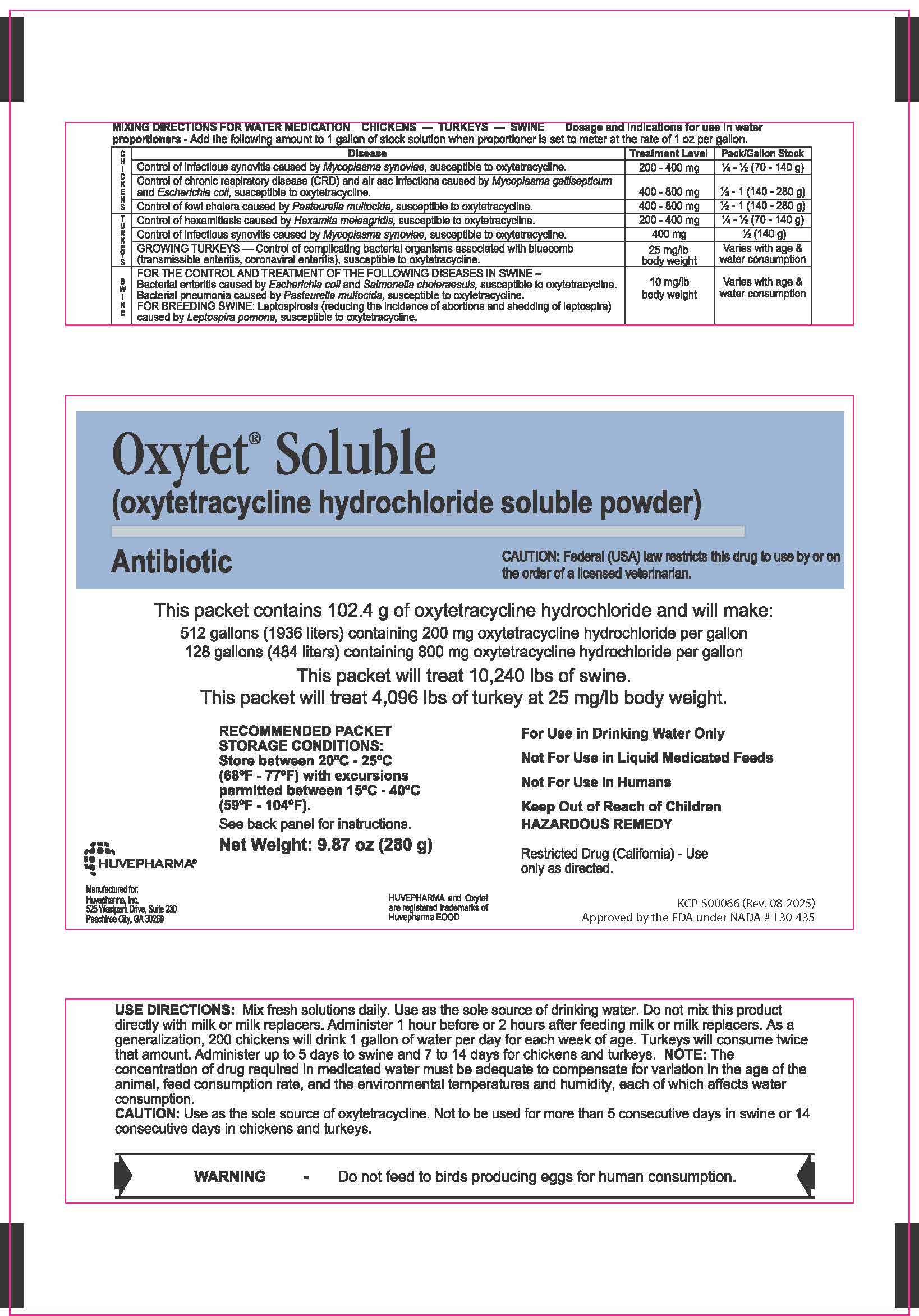 DRUG LABEL: Oxytet
NDC: 23243-6759 | Form: POWDER, FOR SOLUTION
Manufacturer: Huvepharma, Inc
Category: animal | Type: PRESCRIPTION ANIMAL DRUG LABEL
Date: 20251222

ACTIVE INGREDIENTS: OXYTETRACYCLINE HYDROCHLORIDE 0.357 g/1 g

280 GRAM Front Panel

Oxytet® Soluble

(oxytetracycline hydrochloride soluble powder)
Antibiotic

CAUTION: Federal (USA) law restricts this drug to use by or on
the order of a licensed veterinarian.

This packet contains 102.4 g of oxytetracycline hydrochloride and will make:

512 gallons (1936 liters) containing 200 mg oxytetracycline hydrochloride per gallon
128 gallons (484 liters) containing 800 mg oxytetracycline hydrochloride per gallon

This packet will treat 10,240 lbs of swine.
This packet will treat 4,096 lbs of turkey at 25 mg/lb body weight.

RECOMMENDED PACKET STORAGE CONDITIONS:
Store between 20ºC - 25ºC (68ºF - 77ºF) with excursions
permitted between 15ºC - 40ºC (59ºF - 104ºF).
See back panel for instructions.
Net Weight: 9.87 oz (280 g)

For Use in Drinking Water Only

Not For Use in Liquid Medicated Feeds

Not For Use in Humans

Keep Out of Reach of Children

HAZARDOUS REMEDY

Restricted Drug (California) - Use
only as directed.

HUVEPHARMA®

Manufactured for:
Huvepharma, Inc.
525 Westpark Drive, Suite 230
Peachtree City, GA 30269

HUVEPHARMA and Oxytet are registered trademarks of Huvepharma EOOD

KCP-S00066 (Rev. 08-2025)
Approved by FDA under NADA # 130-435

INDICATIONS AND USAGE

USE DIRECTIONS: Mix fresh solutions daily. Use as the sole source of drinking water. Do not mix this product directly with milk or milk replacers. Administer 1 hour before or 2 hours after feeding milk or milk replacers. As a generalization, 200 chickens will drink 1 gallon of water per day for each week of age. Turkeys will consume twice that amount. Administer up to 5 days to swine and 7 to 14 days for chickens and turkeys. NOTE: The concentration of drug required in medicated water must be adequate to compensate for variation in the age of the animal, feed consumption rate, and the environmental temperatures and humidity, each of which affects water consumption.

WARNINGS AND PRECAUTIONS

CAUTION: Use as the sole source of oxytetracycline. Not to be used for more than 5 consecutive days in swine or 14
consecutive days in chickens and turkeys.

WARNINGS AND PRECAUTIONS

WARNING - Do not feed to birds producing eggs for human consumption.

DOSAGE AND ADMINISTRATION

MIXING DIRECTIONS FOR WATER MEDICATION CHICKENS — TURKEYS — SWINE Dosage and indications for use in water proportioners - Add the following amount to 1 gallon of stock solution when proportioner is set to meter at the rate of 1 oz per gallon.

C; H; I; C; K; E; N; S | Disease | Treatment Level | Pack/Gallon Stock
C; H; I; C; K; E; N; S | Control of infectious synovitis caused by Mycoplasma synoviae, susceptible to oxytetracycline. | 200 - 400 mg | ¼ - ½ (70 - 140 g)
C; H; I; C; K; E; N; S | Control of chronic respiratory disease (CRD) and air sac infections caused by Mycoplasma gallisepticum and Escherichia coli, susceptible to oxytetracycline. | 400 - 800 mg | ½ - 1 (140 - 280 g)
C; H; I; C; K; E; N; S | Control of fowl cholera caused by Pasteurella multocida, susceptible to oxytetracycline. | 400 - 800 mg | ½ - 1 (140 - 280 g)
T; U; R; K; E; Y; S | Control of hexamitiasis caused by Hexamita meleagridis, susceptible to oxytetracycline. | 200 - 400 mg | ¼ - ½ (70 - 140 g)
T; U; R; K; E; Y; S | Control of infectious synovitis caused by Mycoplasma synoviae, susceptible to oxytetracycline. | 400 mg | ½ (140 g)
T; U; R; K; E; Y; S | GROWING TURKEYS — Control of complicating bacterial organisms associated with bluecomb (transmissible enteritis, coronaviral enteritis), susceptible to oxytetracycline. | 25 mg/lb body weight | Varies with age & water; consumption
S; W; I; N; E | FOR THE CONTROL AND TREATMENT OF THE FOLLOWING DISEASES IN SWINE – Bacterial enteritis caused by Escherichia coli and Salmonella choleraesuis, susceptible to oxytetracycline. Bacterial pneumonia caused by Pasteurella multocida, susceptible to oxytetracycline. FOR BREEDING SWINE: Leptospirosis (reducing the incidence of abortions and shedding of leptospira) caused by Leptospira pomona, susceptible to oxytetracycline. | 10 mg/lb body weight | Varies with age & water consumption

1400 GRAM Front Panel

Oxytet® Soluble

(oxytetracycline hydrochloride soluble powder)
Antibiotic

CAUTION: Federal (USA) law restricts this drug to use by or on
the order of a licensed veterinarian.

This packet contains 512 g of oxytetracycline hydrochloride and will make:

2560 gallons (9690 liters) containing 200 mg oxytetracycline hydrochloride per gallon
1280 gallons (4845 liters) containing 400 mg oxytetracycline hydrochloride per gallon
640 gallons (2422 liters) containing 800 mg oxytetracycline hydrochloride per gallon

This packet will treat 51,200 lbs of swine.
This packet will treat 20,480 lbs of turkey at 25 mg/lb body weight.

RECOMMENDED PACKET STORAGE CONDITIONS:
Store between 20ºC - 25ºC (68ºF - 77ºF) with excursions
permitted between 15ºC - 40ºC (59ºF - 104ºF).
See back panel for instructions.

Net Weight
3.09 lbs (1400 g)

For Use in Drinking Water Only

Not For Use in Liquid Medicated Feeds

Not For Use in Humans

Keep Out of Reach of Children

HAZARDOUS REMEDY

Restricted Drug (California) - Use
only as directed.

HUVEPHARMA®

Manufactured for:
Huvepharma, Inc.
525 Westpark Drive, Suite 230
Peachtree City, GA 30269

HUVEPHARMA and Oxytet are registered trademarks of
Huvepharma EOOD

13924800 Rev. 02-2021
Approved by FDA under NADA # 130-435

INDICATIONS AND USAGE

USE DIRECTIONS: Mix fresh solutions daily. Use as the sole source of drinking water. Do not mix this product directly with milk or milk replacers. Administer 1 hour before or 2 hours after feeding milk or milk replacers. As a generalization, 200 chickens will drink 1 gallon of water per day for each week of age. Turkeys will consume twice that amount. Administer up to 5 days to swine and 7 to 14 days for chickens and turkeys. NOTE: The concentration of drug required in medicated water must be adequate to compensate for variation in the age of the animal, feed consumption rate, and the environmental temperatures and humidity, each of which affects water consumption.

WARNINGS AND PRECAUTIONS

CAUTION: Use as the sole source of oxytetracycline. Not to be used for more than 5 consecutive days in swine or 14
consecutive days in chickens and turkeys.

WARNINGS AND PRECAUTIONS

Warning - Do not feed to birds producing eggs for human consumption.

Oxytet® Soluble
(oxytetracycline hydrochloride soluble powder)

Antibiotic

DOSAGE AND ADMINISTRATION

MIXING DIRECTIONS FOR WATER MEDICATION CHICKENS — TURKEYS — SWINE Dosage and indications for use in water proportioners - Add 1 pack to the following amount of water to make a stock solution for use in a proportioner set to meter at the rate of one ounce per gallon.

C H I C K E N S | Disease | Treatment Level | Gallons Stock/Pack
C H I C K E N S | Control of infectious synovitis caused by Mycoplasma synoviae, susceptible to oxytetracycline. | 200 - 400 mg | 20 - 10
C H I C K E N S | Control of chronic respiratory disease (CRD) and air sac infections caused by Mycoplasma gallisepticum and Escherichia coli, susceptible to oxytetracycline. | 400 - 800 mg | 10 - 5
C H I C K E N S | Control of fowl cholera caused by Pasteurella multocida, susceptible to oxytetracycline. | 400 - 800 mg | 10 - 5
T U R K E Y S | Control of hexamitiasis caused by Hexamita meleagridis, susceptible to oxytetracycline. | 200 - 400 mg | 20 - 10
T U R K E Y S | Control of infectious synovitis caused by Mycoplasma synoviae, susceptible to oxytetracycline. | 400 mg | 10
T U R K E Y S | GROWING TURKEYS — Control of complicating bacterial organisms associated with bluecomb (transmissible enteritis, coronaviral enteritis), susceptible to oxytetracycline. | 25 mg/lb body weight | Varies with age & water consumption
S W I N E | FOR THE CONTROL AND TREATMENT OF THE FOLLOWING DISEASES IN SWINE – Bacterial enteritis caused by Escherichia coli and Salmonella choleraesuis, susceptible to oxytetracycline. Bacterial pneumonia caused by Pasteurella multocida, susceptible to oxytetracycline. FOR BREEDING SWINE: Leptospirosis (reducing the incidence of abortions and shedding of leptospira) caused by Leptospira pomona, susceptible to oxytetracycline. | 10 mg/lb body weight | Varies with age & water consumption

1772 GRAM Front Panel

Oxytet® Soluble

(oxytetracycline hydrochloride soluble powder)
Antibiotic

CAUTION: Federal (USA) law restricts this drug to use by
or on the order of a licensed veterinarian.

This packet contains 648 g of oxytetracycline hydrochloride and will make:

3240 gallons (12,265 liters) containing 200 mg oxytetracycline hydrochloride per gallon
1620 gallons (6,132 liters) containing 400 mg oxytetracycline hydrochloride per gallon
810 gallons (3,066 liters) containing 800 mg oxytetracycline hydrochloride per gallon

This packet will treat 64,800 lbs of swine.
This packet will treat 25,920 lbs of turkey at 25 mg/lb body weight.

RECOMMENDED PACKET STORAGE CONDITIONS:
Store between 20ºC - 25ºC (68ºF - 77ºF) with excursions
permitted between 15ºC - 40ºC (59ºF - 104ºF).

See back panel for
instructions.

Net Weight
3.91 lbs (1772 g)

For Use in Drinking Water Only

Not For Use in Liquid Medicated Feeds

Not For Use in Humans

Keep Out of Reach of Children

HAZARDOUS REMEDY

Restricted Drug (California) - Use
only as directed.

HUVEPHARMA®

Manufactured for:
Huvepharma, Inc.
525 Westpark Drive, Suite 230
Peachtree City, GA 30269

HUVEPHARMA and Oxytet are registered trademarks of
Huvepharma EOOD.

13925200 (Rev. 02-2021)
Approved by FDA under # 130-435

INDICATIONS AND USAGE

USE DIRECTIONS: Mix fresh solutions daily. Use as the sole source of drinking water. Do not mix this product directly
with milk or milk replacers. Administer 1 hour before or 2 hours after feeding milk or milk replacers. As a
generalization, 200 chickens will drink 1 gallon of water per day for each week of age. Turkeys will consume twice
that amount. Administer up to 5 days to swine and 7 to 14 days for chickens and turkeys. NOTE: The concentration
of drug required in medicated water must be adequate to compensate for variation in the age of the animal, feed
consumption rate, and the environmental temperatures and humidity, each of which affects water consumption.

WARNINGS AND PRECAUTIONS

CAUTION: Use as the sole source of oxytetracycline. Not to be used for more than 5 consecutive days in swine or 14
consecutive days in chickens and turkeys.

WARNINGS AND PRECAUTIONS

WARNING - Do not feed to birds producing eggs for human consumption.

Oxytet® Soluble
(oxytetracycline hydrochloride soluble powder)

Antibiotic

DOSAGE AND ADMINISTRATION

MIXING DIRECTIONS FOR WATER MEDICATION CHICKENS — TURKEYS — SWINE
Dosage and indications for use in water proportioners - Add 1 pack to the following amount of water to make a stock solution for use in a proportioner set to meter at the rate of one ounce per gallon.

C H I C K E N S | Disease | Treatment Level | Gallons Stock/Pack
C H I C K E N S | Control of infectious synovitis caused by Mycoplasma synoviae, susceptible to oxytetracycline. | 200 - 400 mg | 25.3 - 12.6
C H I C K E N S | Control of chronic respiratory disease (CRD) and air sac infections caused by Mycoplasma gallisepticum and Escherichia coli, susceptible to oxytetracycline. | 400 - 800 mg | 12.6 - 6.3
C H I C K E N S | Control of fowl cholera caused by Pasteurella multocida, susceptible to oxytetracycline. | 400 - 800 mg | 12.6 - 6.3
T U R K E Y S | Control of hexamitiasis caused by Hexamita meleagridis, susceptible to oxytetracycline. | 200 - 400 mg | 25.3 - 12.6
T U R K E Y S | Control of infectious synovitis caused by Mycoplasma synoviae, susceptible to oxytetracycline. | 400 mg | 12.6
T U R K E Y S | GROWING TURKEYS — Control of complicating bacterial organisms associated with bluecomb (transmissible enteritis, coronaviral enteritis), susceptible to oxytetracycline. | 25 mg/lb body weight | Varies with age & water consumption
S W I N E | FOR THE CONTROL AND TREATMENT OF THE FOLLOWING DISEASES IN SWINE – Bacterial enteritis caused by Escherichia coli and Salmonella choleraesuis, susceptible to oxytetracycline. Bacterial pneumonia caused by Pasteurella multocida, susceptible to oxytetracycline. FOR BREEDING SWINE: Leptospirosis (reducing the incidence of abortions and shedding of leptospira) caused by Leptospira pomona, susceptible to oxytetracycline. | 10 mg/lb body weight | Varies with age & water consumption